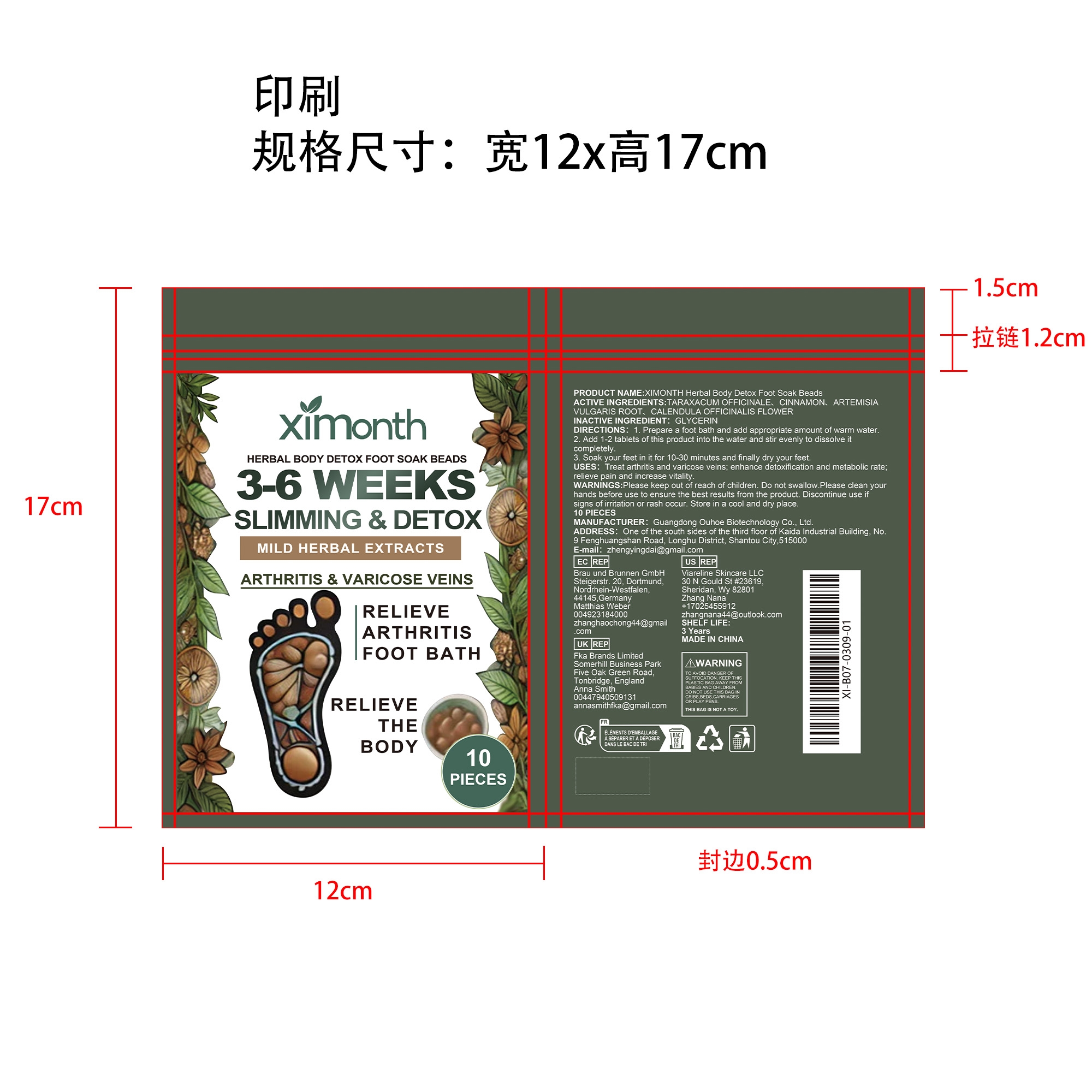 DRUG LABEL: XIMONTH Herbal Body Detox Foot Soak Beads
NDC: 84744-070 | Form: PATCH
Manufacturer: Guangdong Ouhoe Biotechnology Co., Ltd.
Category: otc | Type: HUMAN OTC DRUG LABEL
Date: 20241028

ACTIVE INGREDIENTS: TARAXACUM OFFICINALE 3 g/10 g; ARTEMISIA VULGARIS ROOT 1.5 g/10 g; CALENDULA OFFICINALIS FLOWER 1.5 g/10 g; CINNAMON 1 g/10 g
INACTIVE INGREDIENTS: GLYCERIN 3 g/10 g

ACTIVE INGREDIENTS

TARAXACUM OFFICINALE,CINNAMON,ARTEMISIA VULGARIS ROOT,CALENDULA OFFICINALIS FLOWER

PURPOSE

Treat arthritis and varicose veins; enhance detoxification and metabolic rate;relieve pain and increase vitality. WARNINGS:Please keep out of reach of children. Do not swallow.Please clean yourhands before use to ensure the best results from the product. Discontinue use ifsigns of irritation or rash occur. Store in a cool and dry place.

USE

1. Prepare a foot bath and add appropriate amount of warm water.

2. Add 1-2 tablets of this product into the water and stir evenly to dissolve it completely.

3. Soak your feet in it for 10-30 minutes and finally dry your feet.

WARNINGS

Please keep out of reach of children. Do not swallow.Please clean your hands before use to ensure the best results from the product. Discontinue use if signs of irritation or rash occur. Store in a cool and dry place.

STOP USE

Discontinue use if signs of irritation or rash occur.

DO NOT USE

Discontinue use if signs of irritation or rash occur.

KEEP OUT OF REACH OF CHILDREN

Please keep out of reach of children. Do not swallow.

STORAGE AND HANDLING

Store in a cool and dry place.

INACTIVE INGREDIENT

GLYCERIN